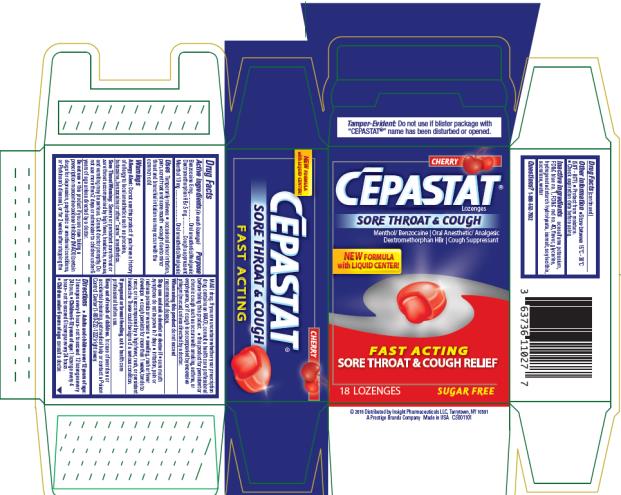 DRUG LABEL: CEPASTAT
NDC: 63736-205 | Form: LOZENGE
Manufacturer: Insight Pharmaceuticals LLC
Category: otc | Type: HUMAN OTC DRUG LABEL
Date: 20241025

ACTIVE INGREDIENTS: MENTHOL 10 mg/1 1; BENZOCAINE 6 mg/1 1; DEXTROMETHORPHAN HYDROBROMIDE 5 mg/1 1
INACTIVE INGREDIENTS: ACESULFAME POTASSIUM; FD&C BLUE NO. 1; FD&C RED NO. 40; GLYCERIN; HYDROGENATED STARCH HYDROLYSATE; ISOMALT; LECITHIN, SOYBEAN; SUCRALOSE; WATER

Cepastat Sore Throat and Cough

Tamper Evident: Do not use if blister package with “CĒPASTAT®” name has been disturbed or opened.

Drug Facts

Active Ingredients (in each lozenge)

Benzocaine 6 mg

Purpose

Oral Anesthetic/Analgesic

Active Ingredients (in each lozenge)

Dextromethorphan HBr 5 mg

Purpose

Cough Suppressant

Active Ingredients (in each lozenge)

Menthol 10 mg

Purpose

Oral Anesthetic/Analgesic

Uses

Temporarily relieves

- occasional minor irritation, pain, sore throat and sore mouth
- cough due to minor throat and bronchial irritation as may occur with the common cold

Warnings

Allergy Alert: Do not use this product if you have a history of allergy to local anesthetics such as procaine, butacaine, benzocaine or other “caine” anesthetics.

Sore Throat Warning: Severe or persistent sore throat or sore throat accompanied by high fever, headache, nausea, and vomiting may be serious. Consult doctor promptly. Do not use more than 2 days or administer to children under 6 years of age unless directed by a doctor.

Do not use

- this product if you are now taking a prescription monoamine oxidase inhibitor (MAOI) (certain drugs for depression, psychiatric or emotional conditions, or Parkinson’s disease), or for 2 weeks after stopping the MAOI drug. If you are uncertain whether your prescription drug contains an MAOI, consult a health care professional before taking this product.
- this product for persistent or chronic cough such as occurs with smoking, asthma, or emphysema, or if cough is accompanied by excessive phlegm (mucus) unless directed by a doctor.

When using this product

do not exceed recommended dosage.

Stop use and ask a dentist or doctor if

- sore mouth symptoms do not improve in 7 days
- irritation, pain or redness persists or worsens
- swelling, rash or fever develops
- cough persists for more than 1 week, tends to recur, or is accompanied by a high fever, rash, or persistent headache. These could be symptoms of a serious condition.

Keep out of reach of children.

In case of overdose or accidental poisoning, get medical help or contact a Poison Control Center right away.

Directions

- Adults and children over 12 years of age: 2 lozenges every 4 hours – not to exceed 12 lozenges every 24 hours.
- Children 6-12 years of age: 1 lozenge every 4 hours – not to exceed 6 lozenges every 24 hours.
- Children under 6 years of age: consult a doctor.

Other information

- Store between 59ºF and 86ºF (15ºC - 30ºC).
- Protect from moisture.
- Check expiration date before using.

Inactive ingredients

acesulfame potassium, FD&C blue no. 1, FD&C red no. 40, flavor, glycerine, hydrogenated starch hydrolysate, isomalt, soy lecithin, sucralose, water

Questions?

1-800-552-7932

PRINCIPAL DISPLAY PANEL

CĒPASTAT®
SORE THROAT & COUGH
Menthol/Benzocaine | Oral Anesthetic/Analgesic
Dextromethorphan HBr 5 mg | Cough Suppressant
FAST ACTING
SORE THROAT & COUGH RELIEF
18 LOZENGES
CHERRY
SUGAR FREE